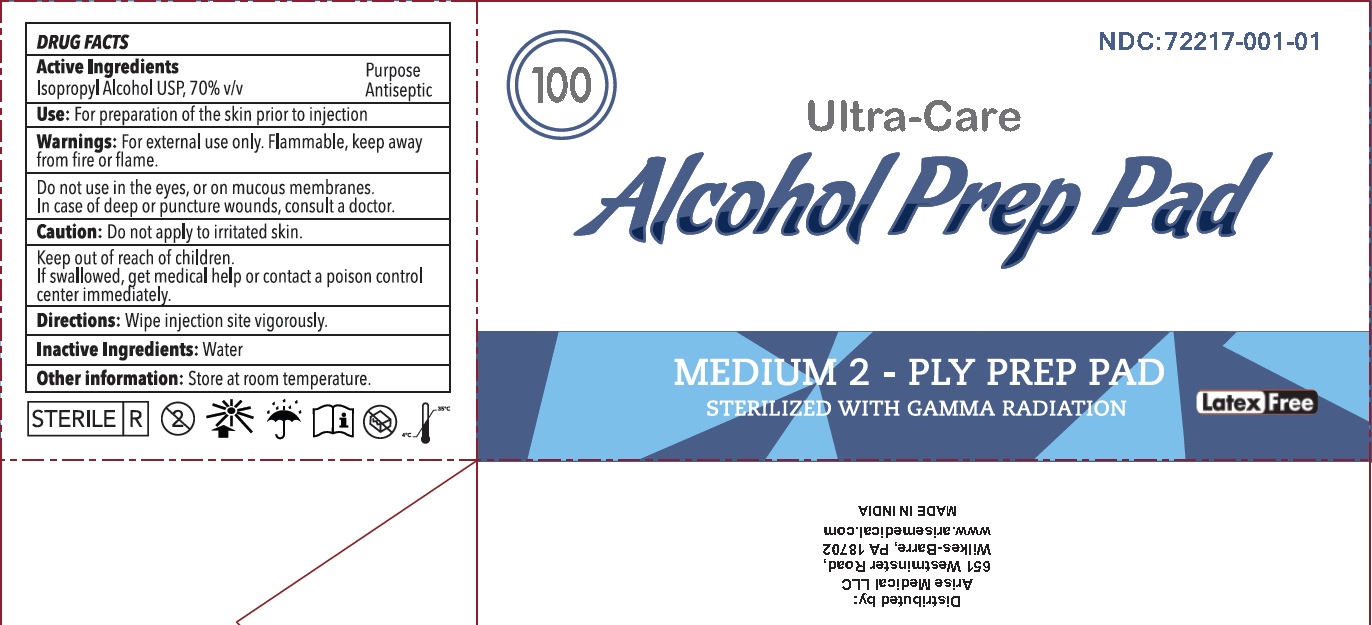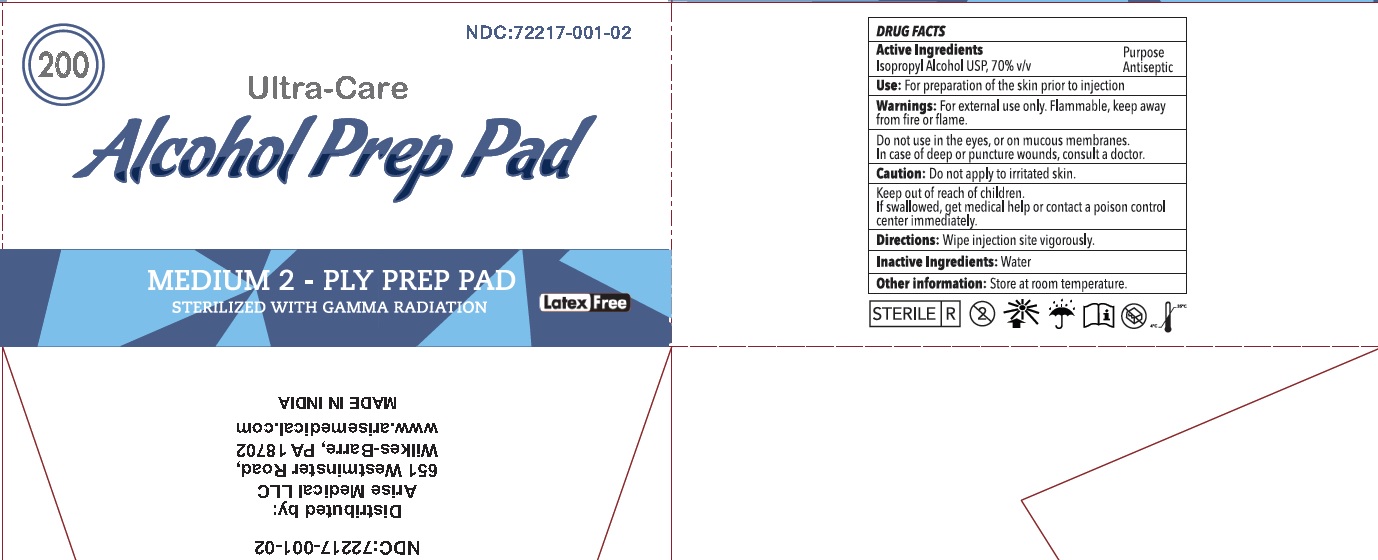 DRUG LABEL: Ultra-Care Alcohol Prep pad
NDC: 72217-001 | Form: SWAB
Manufacturer: Arise Medical LLC
Category: otc | Type: HUMAN OTC DRUG LABEL
Date: 20200128

ACTIVE INGREDIENTS: ISOPROPYL ALCOHOL 70 mL/100 mL
INACTIVE INGREDIENTS: WATER

Active Ingredient

Isopropyl Alcohol, 70% v/v

Purpose

Antiseptic

Use

For preparation of the skin prior to injection

Warnings

For external use only.

Flammable, keep away from fire or flame.

Do not use

in the eyes or on mucous membrane

Consult a Doctor

In case of deep or punctured wounds

Caution

Do not apply to irritated skin

Keep out of reach of children

If swallowed, get medical help or contact a Poison Control Center right away.

Directions

wipe injection site vigorously

Inactive Ingredient

Water

Other Information

Store at room temperature

Principal Display Panel

NDC: 72217-001-01

Ultra-Care Alcohol Prep Pads

MEDIUM 2-PLY PREP PAD

STERILIZED WITH GAMMA RADIATION

Latex FREE

100

NDC: 72217-001-02

Ultra-Care Alcohol Prep Pads

MEDIUM 2-PLY PREP PAD

STERILIZED WITH GAMMA RADIATION

Latex FREE

200